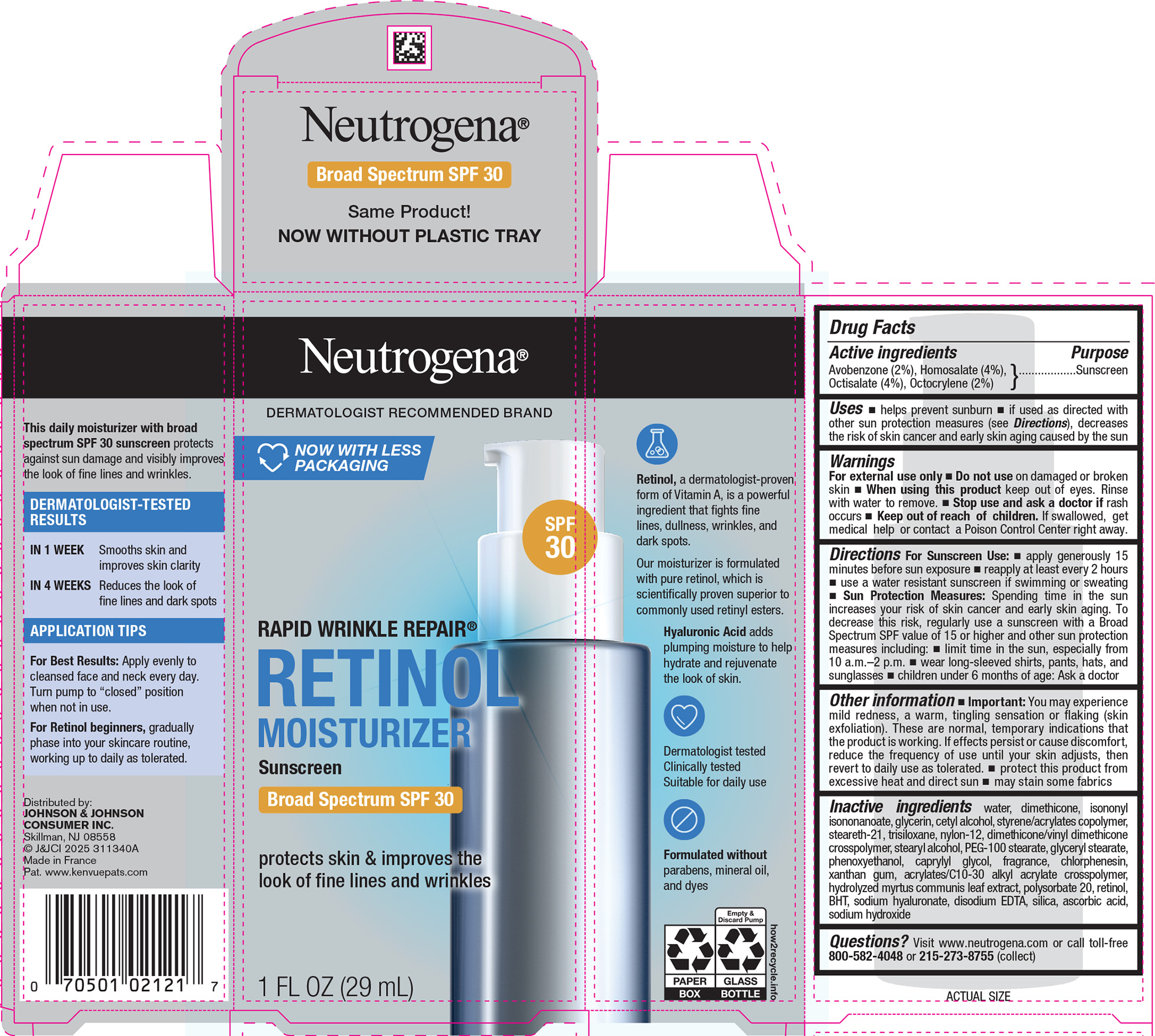 DRUG LABEL: Neutrogena Rapid Wrinkle Repair Retinol Moisturizer Sunscreen Broad Spectrum SPF 30 Day
NDC: 69968-0706 | Form: LOTION
Manufacturer: Kenvue Brands LLC
Category: otc | Type: HUMAN OTC DRUG LABEL
Date: 20251105

ACTIVE INGREDIENTS: AVOBENZONE 20 mg/1 mL; HOMOSALATE 40 mg/1 mL; OCTISALATE 40 mg/1 mL; OCTOCRYLENE 20 mg/1 mL
INACTIVE INGREDIENTS: WATER; DIMETHICONE; ISONONYL ISONONANOATE; GLYCERIN; CETYL ALCOHOL; BUTYL METHACRYLATE/METHYL METHACRYLATE/METHACRYLIC ACID/STYRENE CROSSPOLYMER; STEARETH-21; TRISILOXANE; NYLON-12; DIMETHICONE/VINYL DIMETHICONE CROSSPOLYMER (SOFT PARTICLE); STEARYL ALCOHOL; PEG-100 STEARATE; GLYCERYL MONOSTEARATE; PHENOXYETHANOL; CAPRYLYL GLYCOL; CHLORPHENESIN; XANTHAN GUM; CARBOMER INTERPOLYMER TYPE A (ALLYL SUCROSE CROSSLINKED); POLYSORBATE 20; RETINOL; BUTYLATED HYDROXYTOLUENE; HYALURONATE SODIUM; EDETATE DISODIUM; SILICON DIOXIDE; ASCORBIC ACID; SODIUM HYDROXIDE

NEUTROGENA® RAPID WRINKLE REPAIR® RETINOL MOISTURIZER Sunscreen Broad Spectrum SPF 30 Day

Drug Facts

Active ingredients

Avobenzone (2%), Homosalate (4%), Octisalate (4%), Octocrylene (2%)

Purpose

Sunscreen

Uses

- helps prevent sunburn
- if used as directed with other sun protection measures (see Directions), decreases the risk of skin cancer and early skin aging caused by the sun

Warnings

- For external use only

- Do not use on damaged or broken skin

- When using this product keep out of eyes. Rinse with water to remove.

- Stop use and ask a doctor if rash occurs

- Keep out of reach of children. If swallowed, get medical help or contact a Poison Control Center right away.

Directions

For Sunscreen Use:

- apply generously 15 minutes before sun exposure
- reapply at least every 2 hours
- use a water resistant sunscreen if swimming or sweating
- Sun Protection Measures: Spending time in the sun increases your risk of skin cancer and early skin aging. To decrease this risk, regularly use a sunscreen with a Broad Spectrum SPF value of 15 or higher and other sun protection measures including:
  - limit time in the sun, especially from 10 a.m. – 2 p.m.
  - wear long-sleeved shirts, pants, hats, and sunglasses
  - children under 6 months of age: Ask a doctor

Other information

- You may experience mild redness, a warm, tingling sensation or flaking (skin exfoliation). These are normal, temporary indications that the formula is working. If effects persist/cause discomfort, reduce the frequency of use until your skin adjusts, then revert to daily use as tolerated.
- protect this product from excessive heat and direct sun
- may stain some fabrics

Inactive ingredients

water, dimethicone, isononyl isononanoate, glycerin, cetyl alcohol, styrene/acrylates copolymer, steareth-21, trisiloxane, nylon-12, dimethicone/vinyl dimethicone crosspolymer, stearyl alcohol, PEG-100 stearate, glyceryl stearate, phenoxyethanol, caprylyl glycol, fragrance, chlorphenesin, xanthan gum, acrylates/C10-30 alkyl acrylate crosspolymer, hydrolyzed myrtus communis leaf extract, polysorbate 20, retinol, BHT, sodium hyaluronate, disodium EDTA, silica, ascorbic acid, sodium hydroxide

Questions?

Visit www.neutrogena.com or call toll-free 800-582-4048 or 215-273-8755 (collect)

Distributed by:
JOHNSON & JOHNSON CONSUMER INC.
Skillman, NJ 08558

PRINCIPAL DISPLAY PANEL - 29 mL Bottle Carton

Neutrogena®

DERMATOLOGIST RECOMMENDED BRAND

NOW WITH LESS

PACKAGING

SPF

30

RAPID WRINKLE REPAIR®

RETINOL

MOISTURIZER

Sunscreen

Broad Spectrum SPF 30

protects skin & improves the

look of fine lines and wrinkles

1 FL OZ (29mL)